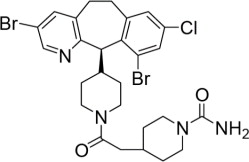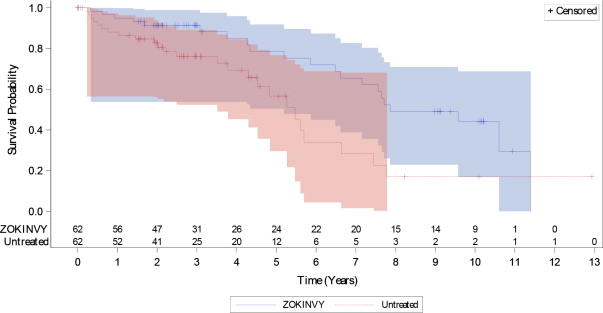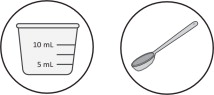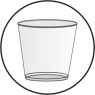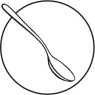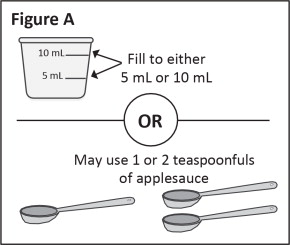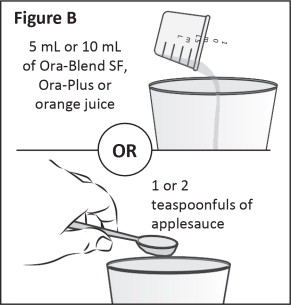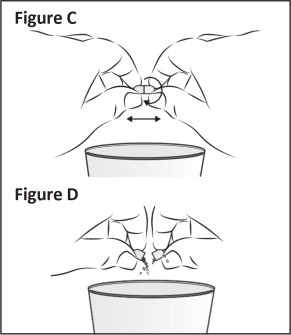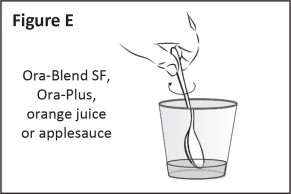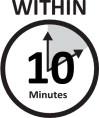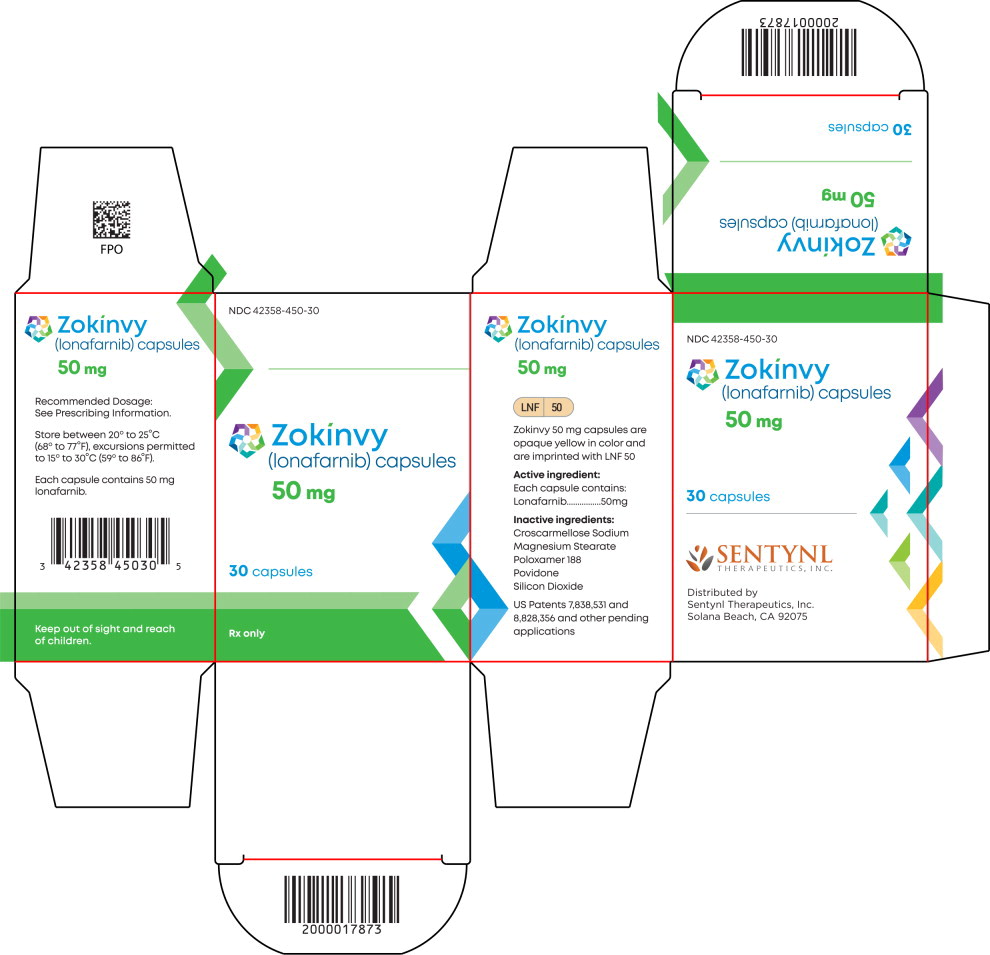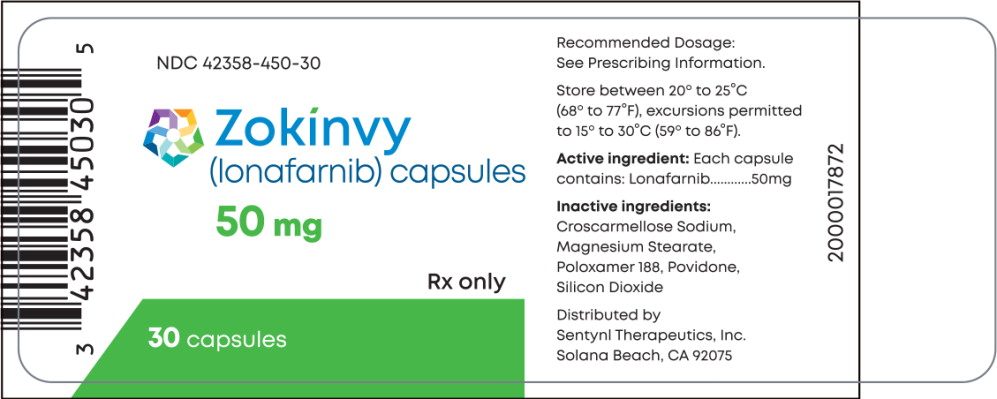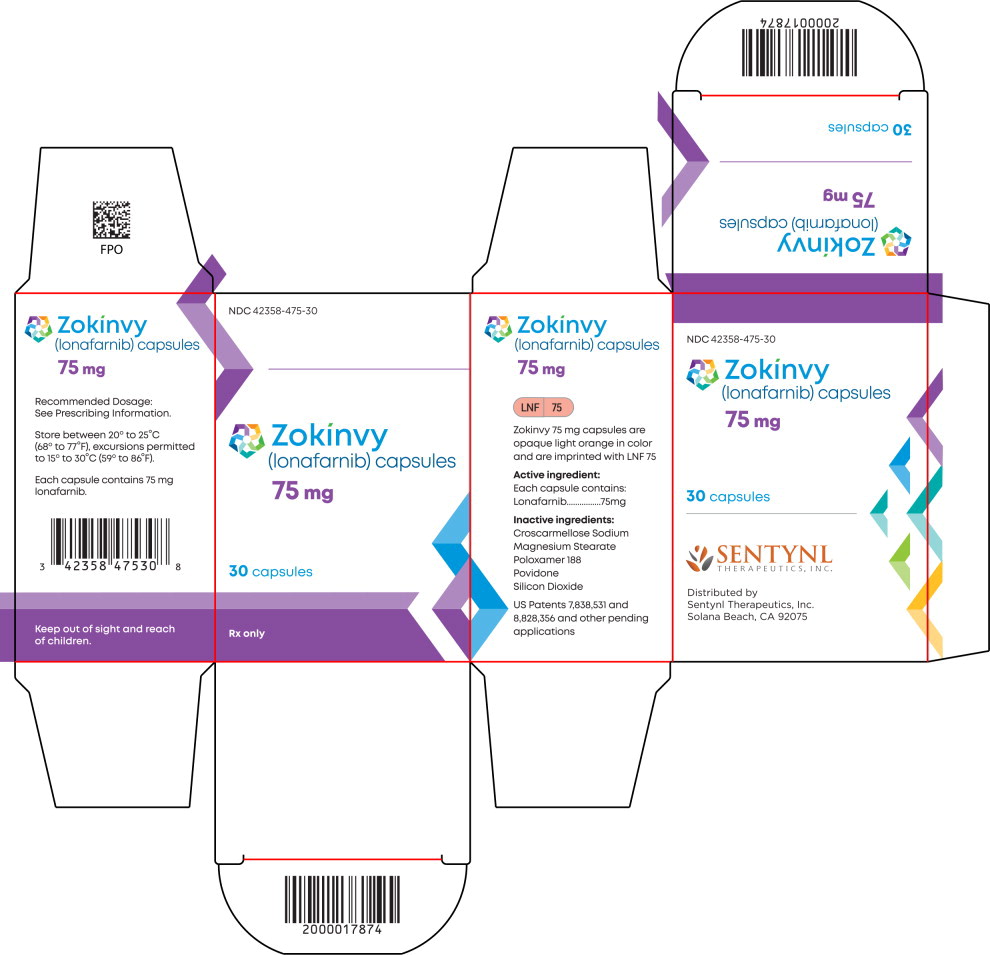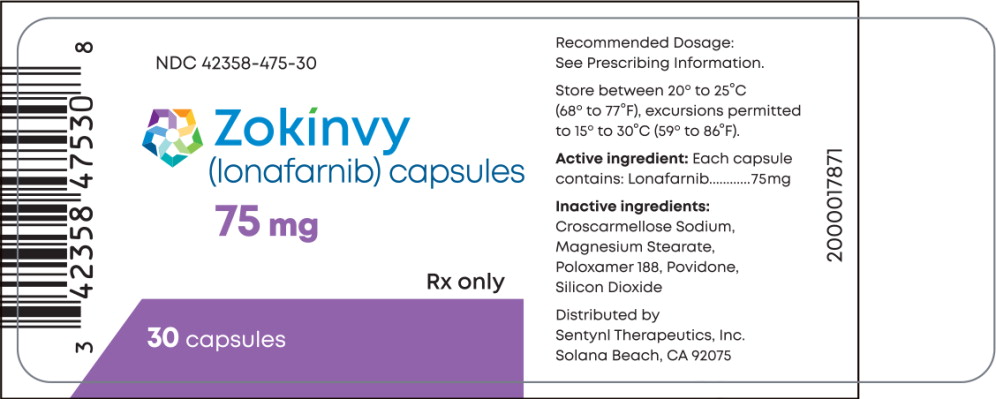 DRUG LABEL: Zokinvy
NDC: 42358-450 | Form: CAPSULE
Manufacturer: Sentynl Therapeutics, Inc.
Category: prescription | Type: HUMAN PRESCRIPTION DRUG LABEL
Date: 20250702

ACTIVE INGREDIENTS: lonafarnib 50 mg/1 1
INACTIVE INGREDIENTS: Povidone 50 mg/1 1; Poloxamer 188 12.50 mg/1 1; Croscarmellose Sodium 10.0 mg/1 1; Silicon Dioxide 1.85 mg/1 1; Magnesium Stearate 0.616 mg/1 1

HIGHLIGHTS OF PRESCRIBING INFORMATION

These highlights do not include all the information needed to use ZOKINVY safely and effectively. See full prescribing information for ZOKINVY.
ZOKINVY® (lonafarnib) capsules, for oral use
Initial U.S. Approval: 2020

RECENT MAJOR CHANGES

Dosage and Administration (2.2) | 3/2024
Warnings and Precautions (5.1) | 3/2024

1 INDICATIONS AND USAGE

ZOKINVY is a farnesyltransferase inhibitor indicated in patients 12 months of age and older with a body surface area of 0.39 m^2 and above: (1)

- To reduce risk of mortality in Hutchinson-Gilford Progeria Syndrome.
- For treatment of processing-deficient Progeroid Laminopathies with either:
  - Heterozygous LMNA mutation with progerin-like protein accumulation.
  - Homozygous or compound heterozygous ZMPSTE24 mutations.

Limitations of Use

Not indicated for other Progeroid Syndromes or processing-proficient Progeroid Laminopathies. Based upon its mechanism of action, ZOKINVY would not be expected to be effective in these populations. (1)

2 DOSAGE AND ADMINISTRATION

- Start at 115 mg/m^2 twice daily with morning and evening meals. (2.1)
- After 4 months, increase to 150 mg/m^2 twice daily. (2.1)
- Round all total daily doses to nearest 25 mg increment. (2.1)
- See full prescribing information for dosage modifications due to adverse reactions. (2.2)
- See full prescribing information for preparation and administration instructions. (2.4)

3 DOSAGE FORMS AND STRENGTHS

Capsules: 50 mg and 75 mg. (3)

4 CONTRAINDICATIONS

- Strong CYP3A inhibitors. (4)
- Strong or moderate CYP3A inducers. (4)
- Midazolam. (2.3, 4)
- Lovastatin, simvastatin, or atorvastatin. (4)

5 WARNINGS AND PRECAUTIONS

- QTc Interval Prolongation: Increases the QTc interval. Avoid use in patients with symptomatic bradycardia, hypokalemia, or hypomagnesemia, and in combination with other drugs known to prolong the QTc interval. (5.1)
- Risk of Reduced Efficacy or Adverse Reactions Due to Drug Interactions: Prior to and during treatment, consider potential for drug interactions and review concomitant medications; monitor for adverse reactions. (5.2, 7)
- Laboratory Abnormalities: Monitor for changes in electrolytes, complete blood counts, and liver enzymes. (5.3)
- Nephrotoxicity: Caused nephrotoxicity in rats. Monitor renal function at regular intervals. (5.4, 13.2)
- Retinal Toxicity: Caused rod-dependent, low-light vision decline in monkeys. Perform ophthalmological evaluation at regular intervals and at the onset of any new visual changes. (5.5, 13.2)
- Impaired Fertility: Caused impaired fertility in female rats, impaired fertility and testicular toxicity in male rats, and toxicity in the male reproductive tract in monkeys. Advise females and males of reproductive potential of the animal fertility findings. (5.6, 13.1, 13.2)
- Embryo-Fetal Toxicity: Can cause fetal harm. Advise females of reproductive potential of the risk to a fetus and to use effective contraception. (5.7, 8.1, 8.3)

6 ADVERSE REACTIONS

The most common adverse reactions (incidence ≥25%) are vomiting, diarrhea, infection, nausea, decreased appetite, fatigue, upper respiratory tract infection, abdominal pain, musculoskeletal pain, electrolyte abnormalities, decreased weight, headache, myelosuppression, increased aspartate aminotransferase, decreased blood bicarbonate, cough, hypertension, and increased alanine aminotransferase. (6.1)

To report SUSPECTED ADVERSE REACTIONS, contact Sentynl Therapeutics, Inc. at 1-888-507-5206 or zokinvysafety@sentynl.com or FDA at 1-800-FDA-1088 or www.fda.gov/medwatch.

7 DRUG INTERACTIONS

- QTc Interval Prolongation Drugs: Avoid concomitant use with ZOKINVY. (2.2, 5.2, 7.1, 12.3)
- See full prescribing information for additional clinically significant drug interactions with ZOKINVY and recommended dosage modifications for drug interactions. (2.2, 7)

FULL PRESCRIBING INFORMATION

1 INDICATIONS AND USAGE

ZOKINVY is indicated in patients 12 months of age and older with a body surface area (BSA) of 0.39 m^2 and above:

- To reduce the risk of mortality in Hutchinson-Gilford Progeria Syndrome (HGPS)
- For the treatment of processing-deficient Progeroid Laminopathies with either:
  - Heterozygous LMNA mutation with progerin-like protein accumulation
  - Homozygous or compound heterozygous ZMPSTE24 mutations

Limitations of Use

ZOKINVY is not indicated for other Progeroid Syndromes or processing-proficient Progeroid Laminopathies. Based upon its mechanism of action, ZOKINVY would not be expected to be effective in these populations.

2 DOSAGE AND ADMINISTRATION

2.1 Recommended Dosage

- The starting dosage of ZOKINVY for patients with a BSA of 0.39 m^2 and above is 115 mg/m^2 twice daily with morning and evening meals (see Table 1) to reduce the risk of gastrointestinal adverse reactions [see Adverse Reactions (6.1)]. An appropriate dosage strength of ZOKINVY is not available for patients with a BSA of less than 0.39 m^2 [see Indications and Usage (1)].
- After 4 months of treatment, increase the dosage to 150 mg/m^2 twice daily with morning and evening meals (see Table 2).
- Round all total daily dosages to the nearest 25 mg increment (see Table 1 and Table 2).
- If a dose is missed, take the dose as soon as possible with food, up to 8 hours prior to the next scheduled dose. If less than 8 hours remain before the next scheduled dose, skip the missed dose, and resume taking ZOKINVY at the next scheduled dose.

Table 1 provides the BSA-based dosage recommendations for the starting dosage of 115 mg/m^2 twice daily.

Table 1: Recommended Dosage and Administration for 115 mg/m^2 Body Surface Area-Based Dosing
BSA (m^2) | Total Daily Dosage Rounded to Nearest 25 mg | Morning Dosing Number of Capsule(s) |  | Evening Dosing Number of Capsule(s)
BSA (m^2) | Total Daily Dosage Rounded to Nearest 25 mg | ZOKINVY 50 mg | ZOKINVY 75 mg | ZOKINVY 50 mg | ZOKINVY 75 mg
0.39 - 0.48 | 100 | 1 |  | 1
0.49 - 0.59 | 125 |  | 1 | 1
0.6 - 0.7 | 150 |  | 1 |  | 1
0.71 - 0.81 | 175 | 2 |  |  | 1
0.82 - 0.92 | 200 | 2 |  | 2
0.93 – 1 | 225 | 1 | 1 | 2

Table 2 provides the BSA-based dosage recommendations for the dosage of 150 mg/m^2 twice daily.

Table 2: Recommended Dosage and Administration for 150 mg/m^2 Body Surface Area-Based Dosing
BSA (m^2) | Total Daily Dosage Rounded to Nearest 25 mg | Morning Dosing Number of Capsule(s) |  | Evening Dosing Number of Capsule(s)
BSA (m^2) | Total Daily Dosage Rounded to Nearest 25 mg | ZOKINVY 50 mg | ZOKINVY 75 mg | ZOKINVY 50 mg | ZOKINVY 75 mg
0.39 - 0.45 | 125 |  | 1 | 1
0.46 - 0.54 | 150 |  | 1 |  | 1
0.55 - 0.62 | 175 | 2 |  |  | 1
0.63 - 0.7 | 200 | 2 |  | 2
0.71 - 0.79 | 225 | 1 | 1 | 2
0.8 - 0.87 | 250 | 1 | 1 | 1 | 1
0.88 - 0.95 | 275 |  | 2 | 1 | 1
0.96 – 1 | 300 |  | 2 |  | 2

2.2 Dosage Modifications Due to Adverse Reactions and Drug Interactions

Table 3: Recommended ZOKINVY Dosage Modifications
Adverse Reaction | Severity | Monitoring and Dose Modifications for ZOKINVY
QTc Interval Prolongation [see Warnings and Precautions (5.1), Drug Interactions (7.1)] | If the QTc interval is greater than or equal to 500 msec | Withhold ZOKINVY until QTc interval is less than 470 msec, then resume ZOKINVY at same dosage. Monitor electrocardiograms (ECGs) prior to initiating ZOKINVY, during treatment, and as clinically indicated.
Gastrointestinal Adverse Reactions [see Adverse Reactions (6.1)] | For patients who have increased their dose of ZOKINVY to 150 mg/m^2 twice daily and are experiencing repeated episodes of vomiting and/or diarrhea resulting in dehydration or weight loss | The dose of ZOKINVY can be reduced to the starting dose of 115 mg/m^2 twice daily (see Table 1). Ensure ZOKINVY is taken with the morning and evening meals and with an adequate amount of water.
CYP3A Drug Interactions [see Warnings and Precautions (5.2), Adverse Reactions (6.1), Drug Interactions (7.1)] | When moderate CYP3A inhibitors are added for a patient already on steady state ZOKINVY | No dosage adjustment for ZOKINVY is recommended.
CYP3A Drug Interactions [see Warnings and Precautions (5.2), Adverse Reactions (6.1), Drug Interactions (7.1)] | When initiating ZOKINVY in a patient who is concurrently on a moderate CYP3A inhibitor | The patient may be at increased risk of adverse reactions. Monitor the patient closely for adverse reactions for at least the first 7 days after initiating ZOKINVY. If the patient experiences an adverse reaction during the first 7 days of the starting dose or thereafter, consider an alternative therapy that is not a moderate CYP3A inhibitor.

2.3 Temporary Discontinuation for Midazolam Use

Temporarily discontinue ZOKINVY for 10 to 14 days before and 2 days after administration of midazolam [see Contraindications (4), Drug Interactions (7.2)].

2.4 Preparation and Administration Instructions

Administer ZOKINVY orally with the morning and evening meals.

Patients Able to Swallow Capsules

- Administer ZOKINVY capsules whole with a sufficient amount of water. Do not chew the capsules.

Patients Unable to Swallow Capsules

- The entire contents of ZOKINVY capsules can be mixed with Ora Blend SF® or Ora-Plus® or, for patients unable to access or tolerate Ora Blend SF or Ora-Plus, the contents of ZOKINVY capsules can be mixed with orange juice or applesauce (see preparation instructions below).
- Do not mix with juice containing grapefruit or Seville oranges [see Contraindications (4), Drug Interactions (7.1)].
- The mixture must be prepared fresh for each dose and taken within approximately 10 minutes of mixing.

Preparation of Dose in Ora Blend SF, Ora-Plus, or Orange Juice

1. For each capsule, empty contents of the capsule into a container containing 5 mL to 10 mL of the liquid.
2. Mix thoroughly with a spoon.
3. Consume entire serving.

Preparation of Dose in Applesauce

1. For each capsule, empty contents of the capsule into a container containing 1 teaspoonful to 2 teaspoonfuls of applesauce.
2. Mix thoroughly with a spoon.
3. Consume entire serving.

3 DOSAGE FORMS AND STRENGTHS

Capsules:

- 50 mg, opaque yellow with “LNF” and “50” printed in black
- 75 mg, opaque light orange with “LNF” and “75” printed in black

4 CONTRAINDICATIONS

ZOKINVY is contraindicated in patients taking:

- Strong CYP3A inhibitors [see Drug Interactions (7.1)]
- Strong or moderate CYP3A inducers [see Drug Interactions (7.1)]
- Midazolam [see Drug Interactions (7.2)]
- Lovastatin, simvastatin, or atorvastatin [see Drug Interactions (7.2)]

5 WARNINGS AND PRECAUTIONS

5.1 QTc Interval Prolongation

ZOKINVY prolongs the QTc interval. Prolongation of the QTc interval increases the risk of Torsade de pointes, other serious arrhythmias, and sudden death.

Avoid use of ZOKINVY in patients with a history of cardiac arrhythmias, as well as in other circumstances that may increase the risk of the occurrence of Torsade de pointes or sudden death, including symptomatic bradycardia, hypokalemia, or hypomagnesemia. Avoid use of ZOKINVY in combination with other drugs known or suspected to prolong the QTc interval [see Drug Interactions (7.1)].

Monitor ECGs prior to initiating ZOKINVY, during treatment, and as clinically indicated. If QTc interval is greater than 500 msec, withhold ZOKINVY until QTc interval is less than 470 msec, then resume ZOKINVY at same dosage.

Obtain serum electrolytes prior to initiating ZOKIVNY and during treatment as clinically indicated. Correct serum electrolyte abnormalities.

5.2 Risk of Reduced Efficacy or Adverse Reactions Due to Drug Interactions

Coadministration of ZOKINVY with other drugs may result in clinically significant drug interactions [see Dosage and Administration (2.2, 2.3), Contraindications (4), Drug Interactions (7.1, 7.2)]. These drug interactions can lead to:

- Reduced efficacy of ZOKINVY
- Increased risk of adverse reactions from ZOKINVY or co-administered drugs

See Table 5 and Table 6 for steps to prevent or manage these clinically significant drug interactions, including dosage recommendations [see Drug Interactions (7.1, 7.2)]. Consider the potential for drug interactions prior to and during ZOKINVY therapy; review concomitant medications during ZOKINVY therapy; and monitor for adverse reactions.

5.3 Laboratory Abnormalities

Some patients treated with ZOKINVY developed laboratory abnormalities [see Adverse Reactions (6.1)]. These included:

- Electrolyte abnormalities (43%), such as hyperkalemia, hypokalemia, hyponatremia, or hypercalcemia
- Myelosuppression (35%), such as reductions in absolute neutrophil count, white blood cell counts, lymphocytes, hemoglobin, or hematocrit
- Increased liver enzymes, such as aspartate aminotransferase (35%), or alanine aminotransferase (27%)

These laboratory abnormalities often improved while continuing ZOKINVY, but it is not possible to exclude ZOKINVY as a cause of the abnormalities. Periodically monitor electrolytes, complete blood counts, and liver enzymes, and manage abnormalities accordingly.

5.4 Nephrotoxicity

Lonafarnib caused nephrotoxicity in rats at plasma drug exposures approximately equal to that achieved with the human dose [see Nonclinical Toxicology (13.2)]. Monitor renal function at regular intervals during ZOKINVY therapy.

5.5 Retinal Toxicity

Lonafarnib caused rod-dependent, low-light vision decline in monkeys at plasma drug exposures similar to that achieved with the human dose [see Nonclinical Toxicology (13.2)]. Perform ophthalmological evaluation at regular intervals and at the onset of any new visual changes during ZOKINVY therapy.

5.6 Impaired Fertility

Lonafarnib caused impaired fertility in female rats at 1.2 times the human dose based on plasma drug exposure [see Nonclinical Toxicology (13.1)].

Lonafarnib caused impaired fertility and testicular toxicity in male rats at 1.5 times the human dose based on plasma drug exposure [see Nonclinical Toxicology (13.1)], and toxicity in the male reproductive tract in monkeys at doses lower than the human dose based on plasma drug exposure [see Nonclinical Toxicology (13.2)].

Advise females and males of reproductive potential of the animal fertility findings, and that the impact on pubertal development and the potential for impaired fertility with ZOKINVY therapy in humans have not been adequately evaluated [see Use in Specific Populations (8.3)].

5.7 Embryo-Fetal Toxicity

Based on findings from animal reproduction studies, ZOKINVY can cause embryo-fetal harm when administered to pregnant women. In animal reproduction studies, oral administration of lonafarnib in pregnant rats during organogenesis produced embryo-fetal toxicity at plasma drug exposures that were approximately equal to the recommended human dose. In pregnant rabbits, oral administration of lonafarnib during organogenesis produced skeletal malformations and variations at exposures lower than the human exposure. Advise pregnant women of the risk to a fetus. Advise females of reproductive potential to avoid becoming pregnant and to use appropriate effective contraception during treatment with ZOKINVY [see Use in Specific Populations (8.1, 8.3)].

6 ADVERSE REACTIONS

6.1 Clinical Trial Experience

Because clinical trials are conducted under widely varying conditions, adverse reaction rates observed in the clinical trials of a drug cannot be directly compared to rates in the clinical trials of another drug and may not reflect the rates observed in practice.

A total of 84 subjects were treated with at least one dose of ZOKINVY with or without additional therapy, of which 8 were treated at a dosage of at least 115 mg/m^2 twice daily for greater than or equal to 10 years.

The safety profile of ZOKINVY is based on 128 patient-years of treatment exposure (62 patients with HGPS and 1 patient with processing-deficient Progeroid Laminopathy with LMNA heterozygous mutation) and pooled results from two Phase 2 open-label, single-arm trials (n=63: 28 patients from Study 1 and 35 treatment naïve patients from Study 2). In Study 1, ZOKINVY treatment was initiated at 115 mg/m^2 twice daily and increased to 150 mg/m^2 twice daily after approximately 4 months for a total treatment duration of 24 to 30 months. Treatment naïve patients in Study 2 received ZOKINVY 150 mg/m^2 twice daily for up to 36 months. In both studies, ZOKINVY was administered orally via capsules or the capsule contents were mixed with Ora Blend SF or Ora-Plus and administered orally as a suspension.

In these two studies, a total of 63 patients received ZOKINVY for a median duration of 2.2 years, with approximately 1.9 years at the recommended dose of 150 mg/m^2 twice daily. The population was 2 to 17 years old, with a similar proportion of males (33 [52%] patients) and females (30 [48%] patients). Most patients had classic HGPS (60 [95%] patients) compared to non-classic HGPS (2 [3%] patients) and 1 (2%) patient had Progeroid Laminopathy with LMNA heterozygous mutation.

Table 4 summarizes adverse reactions reported in the clinical trials. The most common adverse reactions (≥25%) in the clinical trials were vomiting, diarrhea, infection, nausea, decreased appetite, fatigue, upper respiratory tract infection, abdominal pain, musculoskeletal pain, electrolyte abnormalities, decreased weight, headache, myelosuppression, increased aspartate aminotransferase, decreased blood bicarbonate, cough, hypertension, and increased alanine aminotransferase.

Table 4: Adverse Reactions in ≥5% of Patients in Study 1 and Treatment-Naïve Patients in Study 2 Receiving ZOKINVY
Adverse Reactions | ZOKINVY n=63 n (%)
Gastrointestinal disorders
Vomiting | 57 (90%)
Diarrhea | 51 (81%)
Nausea | 35 (56%)
Abdominal pain^1 | 30 (48%)
Constipation | 14 (22%)
Flatulence | 4 (6%)
General disorders and administration site conditions
Fatigue | 32 (51%)
Pyrexia | 9 (14%)
Infections and infestations
Infection^2 | 49 (78%)
Upper respiratory tract infection^3 | 32 (51%)
Rhinitis | 12 (19%)
Investigations
Decreased appetite (anorexia) | 33 (53%)
Electrolyte abnormalities^4 | 27 (43%)
Weight decreased | 23 (37%)
Myelosuppression^5 | 22 (35%)
Increased aspartate aminotransferase | 22 (35%)
Decreased blood bicarbonate | 21 (33%)
Hypertension | 18 (29%)
Increased alanine aminotransferase | 17 (27%)
Dehydration | 3 (5%)
Musculoskeletal and connective tissue disorders
Musculoskeletal pain^6 | 30 (48%)
Nervous system disorders
Headache | 23 (37%)
Cerebral ischemia^7 | 7 (11%)
Ophthalmic
Ocular changes^8 | 15 (24%)
Psychiatric disorders
Depressed mood | 3 (5%)
Respiratory, thoracic and mediastinal disorders
Cough | 21 (33%)
Epistaxis | 13 (21%)
Skin and subcutaneous tissue disorders
Rash | 7 (11%)
Pruritus | 5 (8%)
Mucositis | 5 (8%)
^1Abdominal pain includes stomach pain and abdominal pain.
^2Infection includes abdominal infection, candidiasis, chicken pox, Clostridium difficile colitis, colitis, croup, dengue fever, flu syndrome, flu-like symptoms, fungal infection, gastroenteritis, gastrointestinal infection, Helicobacter pylori infection, infection, infection viral, influenza, nail infection, otitis media, parotitis, perirectal abscess, pneumonia, small intestine infection, submandibular lymphadenitis, tonsillitis, viral infection.
^3Upper respiratory infection includes bronchial infection, bronchitis, sinus infection, and upper respiratory infection.
^4Electrolyte abnormalities include hypermagnesemia, hypokalemia, hyperkalemia, hyponatremia, hypercalcemia, hyperphosphatemia, hypocalcemia, and hypernatremia.
^5Myelosuppression includes absolute neutrophil count decreased, low total white blood cells, lymphopenia, decreased hemoglobin, and hematocrit low.
^6Musculoskeletal pain includes arthritis, back pain, bone pain, foot pain, intercostal pain, joint pain, knee pain, leg pain, musculoskeletal pain, pain in ankle/extremity/fingers/hip/leg/limb/lower limbs/left arm, shoulder pain, unilateral leg pain. Excludes musculoskeletal pain for abdomen.
^7Cerebral ischemia includes cerebral ischemia, central nervous system hemorrhage, and ischemia cerebrovascular.
^8Ocular changes include visual acuity change, corneal clouding, conjunctivitis, watering eyes, keratitis.

Gastrointestinal Adverse Reactions

As noted in Table 4, gastrointestinal adverse reactions were the most frequently reported adverse reactions. Of the 57 patients who experienced vomiting, 30 (53%) patients had mild vomiting (defined as no intervention required), 26 (46%) patients had moderate vomiting (defined as outpatient intravenous hydration; medical intervention required), and 1 (2%) patient had severe vomiting (defined as tube feeding, total parenteral nutrition, or hospitalization indicated). Of the 35 patients who experienced nausea, 34 (97%) patients had mild nausea (defined as loss of appetite without alteration in eating habits) and 1 (3%) patient had moderate nausea (defined as oral intake decreased without significant weight loss, dehydration, or malnutrition). During the first four months of treatment in Study 1, 19 (68%) patients had vomiting and 10 (36%) patients had nausea. By the end of therapy, 4 (14%) patients who were still on ZOKINVY required antiemetics or anti-nauseants. A total of 4 patients discontinued ZOKINVY, mostly due to nausea or vomiting.

Of the 51 patients who experienced diarrhea, the majority of patients (approximately 92%) experienced mild or moderate diarrhea; 38 (75%) patients reported mild diarrhea (defined as an increase of less than 4 stools per day over baseline) and 9 (18%) patients reported moderate diarrhea (defined as an increase of 4 to 6 stools per day over baseline; limiting instrumental activities of daily living). Four (8%) patients reported severe diarrhea (defined as an increase of seven or more stools per day over baseline; hospitalization indicated; severe increase in ostomy output compared to baseline; limiting self-care activities of daily living). During the first four months of treatment in Study 1, 23 (82%) patients had diarrhea; by the end of therapy, 3 (11%) patients had diarrhea. Twelve (43%) patients were treated with loperamide.

Alanine Aminotransferase and Aspartate Aminotransferase Elevations

Increased alanine aminotransferase was commonly reported (17 [27%] patients). Of the 17 patients with increased alanine aminotransferase, 14 (82%) patients had mild increases (defined as greater than upper limit of normal (ULN) to 3.0 times ULN if baseline was normal; 1.5 to 3.0 times ULN if baseline was abnormal), 1 (6%) patient had moderate increases (defined as greater than 3.0 to 5.0 times ULN if baseline was normal or abnormal), and 2 (12%) patients had severe increases (defined as greater than 5.0 to 20.0 times ULN if baseline was normal or abnormal). Increased aspartate aminotransferase was also commonly reported (22 [35%] patients). Of the 22 patients with increased aspartate aminotransferase, 21 (95%) patients had mild increases (defined as greater than ULN to 3.0 times ULN if baseline was normal; 1.5 to 3.0 times ULN if baseline was abnormal) and 1 (5%) patient had a severe increase (defined as greater than 5.0 to 20.0 times ULN if baseline was normal or abnormal). One patient with alanine and aspartate aminotransferase elevations also experienced hypertriglyceridemia and hyperglycemia resulting in discontinuation of ZOKINVY.

Hypertension

Increases in blood pressure have been documented in patients treated with ZOKINVY. At baseline, 22 (35%) patients had either a systolic blood pressure or a diastolic blood pressure or both above the 95th percentile. Over the course of the trials, 18 (29%) patients had hypertension based on systolic blood pressure or diastolic blood pressure measurements above the 95th percentile on 3 or more occasions. Five (8%) patients who were normotensive at baseline had either systolic blood pressure or diastolic blood pressure above the 95th percentile at the end of treatment.

7 DRUG INTERACTIONS

7.1 Effect of Other Drugs on ZOKINVY

Table 5 presents clinically significant drug interactions involving drugs that affect ZOKINVY.

Table 5: Clinically Significant Drug Interactions (Drugs that Affect ZOKINVY)
CYP3A Inhibitors
Clinical Impact | Lonafarnib is metabolized by CYP3A. Concomitant use of ZOKINVY with a strong CYP3A inhibitor may increase lonafarnib area under curve (AUC) and maximum concentration (Cmax) [see Clinical Pharmacology (12.3)], which may increase the incidence and severity of adverse reactions, including QTc interval prolongation. Prolongation of the QTc interval increases the risk of Torsade de pointes, other serious arrhythmias, and sudden death [see Warnings and Precautions (5.1)].
Prevention or Management | Strong CYP3A inhibitors | Use of ZOKINVY with strong CYP3A inhibitors is contraindicated [see Contraindications (4)]. Avoid consumption of grapefruit or Seville oranges.
Prevention or Management | Moderate CYP3A inhibitors | No dosage adjustment for ZOKINVY is recommended when moderate CYP3A inhibitors are added to steady-state ZOKINVY [see Dosage and Administration (2.2)]. When initiating ZOKINVY in a patient who is currently on a moderate CYP3A inhibitor, the patient may be at increased risk of adverse reactions [see Dosage and Administration (2.2)].
CYP3A Inducers
Clinical Impact | Coadministration of ZOKINVY with a strong CYP3A inducer decreases lonafarnib Cmax and AUC [see Clinical Pharmacology (12.3)], which may reduce ZOKINVY efficacy.
Prevention or Management | Strong or moderate CYP3A inducers | Use of ZOKINVY with strong or moderate CYP3A inducers is contraindicated [see Contraindications (4)].
Prevention or Management | Weak CYP3A inducers | No ZOKINVY dosage adjustment is recommended.
QTc Prolongation Drugs
Clinical Implication | ZOKINVY causes QTc interval prolongation [see Clinical Pharmacology (12.2)]. Concomitant use of ZOKINVY with other products that prolong the QTc interval may result in a greater increase of the QTc interval and adverse reactions associated with QTc interval prolongation, including Torsade de pointes, other serious arrythmias, and sudden death [see Warnings and Precautions (5.1)].
Prevention or Management | Avoid concomitant use of ZOKINVY with other drugs with a known potential to prolong the QTc interval. If concomitant use cannot be avoided, obtain ECGs when initiating, during concomitant use, and as clinically indicated [see Warnings and Precautions (5.1)].

7.2 ZOKINVY's Effect on Other Drugs

Table 6 presents clinically significant drug interactions involving drugs affected by ZOKINVY.

Table 6: Clinically Significant Drug Interactions (Drugs Affected by ZOKINVY)
CYP3A Substrates
Clinical Impact | Lonafarnib is a strong CYP3A mechanism-based inhibitor. Coadministration of ZOKINVY with a CYP3A substrate increases the AUC and Cmax of the CYP3A substrate [see Clinical Pharmacology (12.3)] which may increase the risk of the CYP3A substrate's adverse reactions, including myopathy or rhabdomyolysis (with statins), or extreme sedation or respiratory depression (with midazolam).
Prevention or Management | HMG CoA reductase inhibitors (“Statins”) | Coadministration of ZOKINVY with lovastatin, simvastatin, or atorvastatin is contraindicated [see Contraindications (4)].
Prevention or Management | Midazolam | Coadministration of ZOKINVY with midazolam is contraindicated [see Contraindications (4)]. Temporarily discontinue ZOKINVY for 10-14 days before and 2 days after administration of midazolam [see Dosage and Administration (2.3)].
Prevention or Management | Other sensitive CYP3A substrates | Avoid coadministration of ZOKINVY with sensitive CYP3A substrates. As noted above, use with lovastatin, simvastatin, or atorvastatin, and midazolam is contraindicated [see Contraindications (4)]). If coadministration of other sensitive CYP3A substrates is unavoidable, monitor for adverse reactions and reduce the dosage of those sensitive CYP3A substrate(s) in accordance with their approved product labeling.
Prevention or Management | Certain CYP3A substrates | When ZOKINVY is coadministered with certain CYP3A substrates where minimal concentration changes may lead to serious or life-threatening toxicities, monitor for adverse reactions and reduce the dosage of the CYP3A substrate in accordance with its approved product labeling.
Loperamide
Clinical Impact | Lonafarnib is a weak inhibitor of P-gp and strong inhibitor of CYP3A. Coadministration of ZOKINVY with loperamide increases the AUC and Cmax of loperamide [see Clinical Pharmacology (12.3)] which may increase the risk of loperamide's adverse reactions.
Prevention or Management | Loperamide is contraindicated in patients less than 2 years of age. When ZOKINVY is coadministered with loperamide, do not exceed loperamide 1 mg once daily when first coadministered. Slowly increase loperamide dosage with caution in accordance with its approved product labeling.
CYP2C19 Substrates
Clinical Impact | Lonafarnib is a moderate CYP2C19 inhibitor. Coadministration of ZOKINVY with a CYP2C19 substrate increases the AUC and Cmax of the CYP2C19 substrate [see Clinical Pharmacology (12.3)] which may increase the risk of the CYP2C19 substrate's adverse reactions.
Prevention or Management | Avoid coadministration of ZOKINVY with CYP2C19 substrates. If coadministration is unavoidable, monitor for adverse reactions and reduce the dosage of the CYP2C19 substrate in accordance with its approved product labeling.
P-gp Substrates
Clinical Impact | Lonafarnib is a weak P-gp inhibitor. Coadministration of ZOKINVY with a P-gp substrate increases the AUC and Cmax of the P-gp substrate [see Clinical Pharmacology (12.3)], which may increase the risk of the P-gp substrate's adverse reactions.
Prevention or Management | When ZOKINVY is coadministered with P-gp substrates (e.g., digoxin, dabigatran) where minimal concentration changes may lead to serious or life-threatening toxicities, monitor for adverse reactions and reduce the dosage of the P-gp substrate in accordance with its approved product labeling.

8 USE IN SPECIFIC POPULATIONS

8.1 Pregnancy

Risk Summary

Based on findings from animal studies, ZOKINVY can cause embryofetal harm when administered to a pregnant woman. There are no human data on ZOKINVY use in pregnant women to evaluate for a drug-associated risk of major birth defects, miscarriage or adverse maternal or fetal outcomes. Advise pregnant women of the risk to a fetus.

In animal reproduction studies, oral administration of lonafarnib to pregnant rats during organogenesis produced embryo-fetal toxicity at exposures that were 1.2-times the human exposure at the recommended dose of 150 mg/m^2 twice daily. In pregnant rabbits, oral administration of lonafarnib during organogenesis produced skeletal malformations and variations at exposures lower than the human exposure at 150 mg/m^2 twice daily, and maternal toxicity at 26 times the human exposure at 150 mg/m^2 twice daily (see Data).

The estimated background risk of major birth defects and miscarriage for the indicated population is unknown. All pregnancies have a background risk of birth defect, loss, or other adverse outcomes. In the U.S. general population, the estimated background risk of major birth defects and miscarriage in clinically recognized pregnancies is 2 to 4% and 15 to 20%, respectively.

Data

Animal Data

In an embryo-fetal development study in rats, oral administration of lonafarnib during organogenesis produced an increase in post-implantation loss (resorptions) and decreases in fetal body weight and number of live fetuses at 30 mg/kg/day (1.2 times the AUC [area under the plasma concentration-time curve] in humans at the recommended dose of 150 mg/m^2 twice daily). No effects on embryo-fetal development in rats were observed at systemic exposures lower than the human AUC at 150 mg/m^2 twice daily.

In rabbits, oral administration of lonafarnib during organogenesis resulted in skeletal malformations and variations at systemic exposures lower than the human AUC at the recommended dose of 150 mg/m^2 twice daily, and maternal toxicity (body weight loss and abortion) at 120 mg/kg/day (26 times the human AUC at 150 mg/m^2 twice daily).

No effects in offspring were observed in a pre- and postnatal development study in rats with maternal administration of up to 20 mg/kg/day orally (AUC lower than the human AUC at 150 mg/m^2 twice daily) during organogenesis through lactation.

8.2 Lactation

Risk Summary

There are no data on the presence of ZOKINVY in human milk, the effects on the breastfed infant, or the effects on milk production. Lonafarnib is excreted in rat milk (see Data). When a drug is present in animal milk, it is likely that the drug will be present in human milk.

The developmental and health benefits of breastfeeding should be considered along with the mother's clinical need for ZOKINVY and any potential adverse effects of the breastfed infant from ZOKINVY or from the underlying maternal condition.

Data

Lonafarnib is excreted in milk following oral administration in lactating rats, with a mean milk to plasma concentration ratio of 1.5 at 12 hours.

8.3 Females and Males of Reproductive Potential

Contraception

ZOKINVY can cause embryo-fetal harm when administered to pregnant women [see Use in Specific Populations (8.1)]. Advise females of reproductive potential to use appropriate effective contraception during treatment with ZOKINVY.

Infertility

Based on findings in rats, ZOKINVY may reduce fertility in females and males of reproductive potential [see Warnings and Precautions (5.6), Nonclinical Toxicology (13.1)].

8.4 Pediatric Use

The safety and effectiveness of ZOKINVY for the treatment of HGPS and processing-deficient Progeroid Laminopathies (with either heterozygous LMNA mutation with progerin-like protein accumulation or homozygous or compound heterozygous ZMPSTE24 mutations) have been established in pediatric patients 12 months of age and older. Use of ZOKINVY for these indications is supported by adequate and well-controlled studies in pediatric patients 2 years of age and older [see Clinical Studies (14)].

The safety and effectiveness of ZOKINVY in pediatric patients less than 12 months of age have not been established.

8.6 Adult Use

The safety and effectiveness of ZOKINVY for the treatment of HGPS and processing-deficient Progeroid Laminopathies (with either heterozygous LMNA mutation with progerin-like protein accumulation or homozygous or compound heterozygous ZMPSTE24 mutations) have been established in adults. Use of ZOKINVY in adults for these indications is based on adequate and well-controlled studies in pediatric patients 2 years of age and older [see Clinical Studies (14)].

11 DESCRIPTION

ZOKINVY (lonafarnib) is a farnesyltransferase inhibitor. The chemical name for lonafarnib is 4-[2-[4-[(11R)-3,10-dibromo-8-chloro-6,11-dihydro-5H- benzo[1,2] cyclohepta [2,4-b]pyridin-11-yl]piperidin-1-yl]-2- oxoethyl]piperidine-1-carboxamide. Its molecular formula is C27H31Br2ClN4O2, molecular mass is 638.8 g/mol, and its chemical structure is depicted below.

ZOKINVY (lonafarnib) capsules for oral administration contain 50 mg or 75 mg of lonafarnib as the active ingredient and the following inactive ingredients: croscarmellose sodium, magnesium stearate, poloxamer 188, povidone, and silicon dioxide. The capsule shells of both strengths contain gelatin, titanium dioxide, and yellow iron oxide; the 75 mg capsule also contains red iron oxide. The imprinting ink contains ammonia solution, black iron oxide, butyl alcohol, dehydrated alcohol, isopropyl alcohol, potassium hydroxide, propylene glycol, purified water, and shellac.

12 CLINICAL PHARMACOLOGY

12.1 Mechanism of Action

Lonafarnib inhibits farnesyltransferase to prevent farnesylation and subsequent accumulation of progerin and progerin-like proteins in the inner nuclear membrane.

12.2 Pharmacodynamics

Cardiac Electrophysiology

The effect of lonafarnib on the QTc interval was evaluated in a randomized, double-blind, placebo- and positive-controlled (moxifloxacin 400 mg single dose), multiple-dose, QTc study in 64 healthy subjects. Subjects received 200 mg lonafarnib twice daily for 9 consecutive days and a single 200 mg dose in the morning on Day 10, with food.

The largest mean increase in QTc interval was 19 msec (upper bound of 90% confidence interval = 27 msec) on Day 10 at 48 hours after administration of the morning dose of lonafarnib 200 mg. The Cmax on Day 10 was 2233 ng/mL, which is similar to the mean Cmax of 2695 ng/mL observed in the HGPS patient population [see Clinical Pharmacology (12.3)].

12.3 Pharmacokinetics

The pharmacokinetics of lonafarnib at steady state in patients with HGPS following oral administration of lonafarnib twice daily with food are summarized in Table 7.

Table 7: Summary of Pharmacokinetic Parameters of Lonafarnib at Steady State after Oral Administration Twice Daily to Patients with HGPS
Lonafarnib Dose |  | Median (range) tmax (hr) | Mean (SD) Cmax (ng/mL) | Mean (SD) AUC 0-8hr (ng*hr/mL) | Mean (SD) AUCtau (ng*hr/mL)
115 mg/m^2 | N | 23 | 23 | 23 | 15
115 mg/m^2 | Results | 2 (0, 6) | 1777 (1083) | 9869 (6327) | 12365 (9135)
150 mg/m^2 | N | 18 | 18 | 18 | 8
150 mg/m^2 | Results | 4 (0, 12) | 2695 (1090) | 16020 (4978) | 19539 (6434)

Absorption

The absolute bioavailability of lonafarnib following oral administration has not been determined. Following oral administration of lonafarnib 75 mg and 100 mg twice daily in healthy subjects under fasted conditions, the geometric mean (CV%) maximum peak plasma concentrations of lonafarnib were 834 (32%) ng/mL and 964 (32%) ng/mL, respectively.

Effect of Food

Following a single oral dose of 75 mg lonafarnib in healthy subjects, the Cmax decreased 55% and AUC decreased 29% with a high-fat meal (approximately 43% fat of the total 952 calories) compared to fasted conditions. Cmax decreased 25% and AUC decreased 21% with a low-fat meal (approximately 12% fat of the total 421 calories) compared to fasted conditions.

Distribution

In vitro plasma protein binding of lonafarnib was greater than or equal to 99% over the concentration range between 0.5 to 40.0 μg/mL. The apparent volumes of distribution were 87.8 L and 97.4 L, respectively, at steady state following oral administration of lonafarnib 100 mg and 75 mg twice daily in healthy subjects.

Elimination

The mean half-life was approximately 4 to 6 hours following oral administration of lonafarnib 100 mg twice daily in healthy subjects.

Metabolism

Lonafarnib is primarily metabolized by CYP3A and to a lesser extent by CYP1A2, CYP2A6, CYP2C8, CYP2C9, CYP2C19, and CYP2E1 in vitro.

In a Phase 1 study in healthy subjects, autoinhibition activity of lonafarnib was demonstrated following repeated dosing of lonafarnib. Specifically, the clearance of lonafarnib following multiple-dose lonafarnib administration was reduced by 75% compared with that following single-dose lonafarnib administration.

Excretion

Following an oral administration of 104 mg [^14C]-lonafarnib under fasted conditions in healthy subjects, approximately 62% of the total radiolabeled dose was recovered in feces and <1% of the total radiolabeled dose was recovered in urine up to 240 hours post-dose. The two most predominant metabolites were HM17 and HM21 (an active metabolite) accounting for 15% and 14% of plasma radioactivity, respectively.

Specific Populations

Patients with Renal Impairment or Hepatic Impairment

ZOKINVY has not been studied in patients with renal impairment or in patients with hepatic impairment.

Male and Female Patients

Following a single oral dose of 100 mg lonafarnib in healthy subjects, the plasma lonafarnib AUC and Cmax were 44% and 26% higher in female subjects, respectively, compared to male subjects. The observed exposure difference by sex in healthy subjects is not considered clinically meaningful.

Geriatric Patients

Following a single oral dose of 100 mg lonafarnib in healthy subjects, the plasma lonafarnib AUC and Cmax were 59% and 27% higher in subjects ≥65 years, respectively, compared to subjects 18 to 45 years of age. The observed higher exposure in geriatric subjects is not considered clinically relevant.

Drug Interaction Studies

In Vitro Studies

Lonafarnib is a CYP3A substrate and a potent CYP3A time-dependent and mechanism-based inhibitor. Lonafarnib is an inhibitor of CYP2C8 and CYP2C19. Lonafarnib is not considered an inhibitor of CYP1A2, CYP2B6, CYP2C8, CYP2C9, or CYP2D6. Lonafarnib is unlikely to be an inducer of CYP1A2, CYP2B6, and CYP3A.

Lonafarnib is not a substrate of transporters OATP1B1, OATP1B3, or BCRP, but is likely a marginal substrate of P-gp. Lonafarnib is an inhibitor of P-gp, OATP1B1, OATP1B3, and BCRP.

Clinical Studies: Effects of other Drugs on Lonafarnib

CYP3A inhibitors

Lonafarnib is a sensitive substrate for CYP3A. With coadministration of a single oral dose of 50 mg lonafarnib following 200 mg ketoconazole (a strong CYP3A inhibitor) once daily for 5 days, the Cmax and AUC of lonafarnib were increased by 270% and 425%, respectively, as compared to lonafarnib administered alone in healthy subjects [see Dosage and Administration (2.2), Contraindications (4), Drug Interactions (7.1)].

Fluconazole

Coadministration of steady-state lonafarnib with multiple-dose fluconazole (a moderate inhibitor of CYP3A and CYP2C9) did not increase lonafarnib Cmax or AUC, as compared to lonafarnib administered alone in healthy subjects. [see Dosage and Administration (2.2), Drug Interactions (7.1)].

CYP3A inducers

With coadministration of a single oral dose of 50 mg lonafarnib (combined with a single oral dose of 100 mg ritonavir) following 600 mg rifampin once daily for 8 days, the Cmax of lonafarnib was reduced by 92% and the AUC was reduced by 98%, as compared to without rifampin coadministration in healthy subjects [see Contraindications (4), Drug Interactions (7.1)].

Clinical Studies: Effects of Lonafarnib on other Drugs

CYP3A Substrates

Lonafarnib is a strong inhibitor of CYP3A. With coadministration of a single oral dose of 3 mg midazolam with multiple oral doses of 100 mg lonafarnib twice daily for 5 days in healthy subjects, the Cmax and AUC of midazolam were increased by 180% and 639%, respectively [see Dosage and Administration (2.3), Contraindications (4), Drug Interactions (7.2)].

Loperamide

With coadministration of a single oral 2 mg dose of loperamide (primarily metabolized by CYP2C8 and CYP3A and a substrate of P-gp) with multiple oral doses of lonafarnib 100 mg twice daily for 5 days in healthy subjects, the Cmax and AUC of loperamide were increased by 214% and 299%, respectively [see Drug Interactions (7.2)].

CYP2C19 Substrates

Lonafarnib is a moderate CYP2C19 inhibitor. With coadministration of a single oral dose of 40 mg omeprazole with multiple oral doses of lonafarnib 75 mg twice daily for 5 days in healthy subjects, the Cmax and AUC of omeprazole were increased by 28% and 60%, respectively [see Drug Interactions (7.2)].

P-gp and OATP1B Substrates

With coadministration of a single oral dose of 180 mg fexofenadine (a P-gp and OATP1B substrate) with multiple oral doses of 100 mg lonafarnib twice daily for 5 days in healthy subjects, the Cmax and AUC of fexofenadine were increased by 21% and 24%, respectively [see Drug Interactions (7.2)].

13 NONCLINICAL TOXICOLOGY

13.1 Carcinogenesis, Mutagenesis, Impairment of Fertility

Carcinogenesis

Carcinogenicity studies have not been conducted with lonafarnib.

Mutagenesis

Lonafarnib was not genotoxic in the bacterial mutagenicity (Ames) assay, in vitro chromosomal aberration assay in mammalian cells, or in vivo micronucleus assay in mice.

Impairment of Fertility

Lonafarnib produced impaired fertility in male rats at 90 mg/kg/day or higher (1.5 times the AUC in humans at the recommended dose of 150 mg/m^2 twice daily), with a nearly complete loss of fertility at 180 mg/kg/day (3 times the AUC in humans). Male rats treated with 180 mg/kg/day exhibited small testes, flaccid testes, and discolored epididymis (84%, 56%, and 24% of males, respectively). No effects on fertility occurred in males at systemic exposures lower than the human AUC at 150 mg/m^2 twice daily.

Female rats treated with 30 mg/kg/day lonafarnib or higher (1.2 times the human AUC at the recommended human dose of 150 mg/m^2 twice daily) showed a decrease in fertility, as indicated by reductions in the number of corpora lutea and implantation sites and increases in pre- and post-implantation loss. No effects on fertility occurred in females at systemic exposures lower than the human AUC at 150 mg/m^2 twice daily [see Warnings and Precautions (5.6)].

13.2 Animal Toxicology and/or Pharmacology

Renal toxicity occurred in a 6-month oral toxicity study of lonafarnib in rats, with kidney lesions (interstitial necrosis and mineralization in the inner medulla) and correlating changes in clinical chemistry (e.g., hyperphosphatemia, hyperkalemia) and urinalysis parameters observed at systemic exposures approximately equal to the AUC in humans at the recommended dose of 150 mg/m^2 twice daily. No evidence of renal toxicity was observed at systemic exposures lower than the human AUC at 150 mg/m^2 twice daily [see Warnings and Precautions (5.4)].

Toxicity in the male reproductive tract occurred in a 1-year oral toxicity study in monkeys at 10 mg/kg/day or higher (AUC lower than the human AUC at the recommended dose of 150 mg/m^2 twice daily). The lesions in the male reproductive tract included aspermia in the epididymis and atrophy of seminiferous tubules, seminal vesicle, and prostate gland. Testicular toxicity was also observed in rats, where severe impairment of male fertility occurred [see Warnings and Precautions (5.6), Nonclinical Toxicology (13.1)].

Ocular (retinal) toxicity occurred in a 1-year oral toxicity study in monkeys at 40 mg/kg/day (3.7 times the human AUC at the recommended dose of 150 mg/m^2 twice daily). The retinal injury involved single cell necrosis of photoreceptor cells in the layer of rods and cones and the outer nuclear layer. No retinal toxicity was observed at 20 mg/kg/day (2.1 times the human AUC at 150 mg/m^2 twice daily). However, in a follow-up study of lonafarnib effects on visual function in monkeys as evaluated by electroretinography, oral administration of 15 mg/kg/day for 13 weeks or 60 mg/kg/day for 6 weeks produced adverse effects on rod-dependent, low-light vision. The effects were observed at several time-points throughout the treatment period. No histological changes in the retina were observed at study termination [see Warnings and Precautions (5.5)].

14 CLINICAL STUDIES

The efficacy of ZOKINVY is based on results from the Observational Cohort Survival Study, which retrospectively compared survival data from two Phase 2 studies in patients with HGPS to those from a natural history cohort.

Study 1 (NCT00425607) was a Phase 2 open-label, single-arm trial that evaluated the efficacy of ZOKINVY in 28 patients (26 with classic HGPS, one with non-classic HGPS, and one with processing-deficient Progeroid Laminopathy with LMNA heterozygous mutation with progerin-like protein accumulation). Patients received ZOKINVY for 24 to 30 months. Patients initiated treatment with ZOKINVY 115 mg/m^2 twice daily. After 4 months of treatment, patients who tolerated treatment had an increase in dose to 150 mg/m^2 twice daily. Among the 28 patients treated, 27 patients with HGPS (16 females, 11 males) were included in the survival assessment. The median age at treatment initiation for the 27 patients was 7.5 years (range: 3 to 16 years). The body weight range was 6.6 to 17.6 kg and the BSA range was 0.38 to 0.75 m^2 (ZOKINVY is not indicated in patients with a BSA less than 0.39 m^2 because the appropriate dosage strength is not available for this population).

Following completion of Study 1, 26 patients enrolled in a second Phase 2 open label, single-arm trial (Study 2, NCT00916747) which consisted of two study phases. In the first phase of Study 2, patients received ZOKINVY with additional therapies for about 5 years. In the second phase of Study 2, patients received ZOKINVY 150 mg/m^2 twice daily for a period of up to 3 years.

There were 35 treatment naïve patients with HGPS enrolled into the second phase of Study 2. Among the 35 treated patients (22 males, 13 females), 34 (97.1%) patients had classic HGPS and 1 (2.9%) patient had non-classic HGPS. The median age was 6 years (range: 2 to 17 years). The body weight range was 6.7 to 22 kg and the BSA range was 0.42 to 0.90 m^2.

Throughout Study 1 and Study 2, ZOKINVY was administered orally via capsules or the capsule contents were mixed with Ora Blend SF or Ora-Plus and administered orally as a suspension.

The retrospective survival analysis was based on the mortality data from 62 treated patients (27 patients in Study 1 and 35 treatment-naïve patients in Study 2) and data from matched, untreated patients in a separate natural history cohort. The mean lifespan of HGPS patients treated with ZOKINVY increased by an average of 3 months through the first three years of follow-up and 2.5 years through the last follow-up time (11 years) compared to untreated patients. The survival analysis summary is provided in Table 8 and Figure 1.

Table 8: Survival Analysis Summary for Patients with HGPS
 | Follow-up time censored at 3-years |  | Last follow-up time
Summary | Untreated (n=62) | ZOKINVY^1 (n=62) | Untreated (n=62) | ZOKINVY^1 (n=62)
Number of Deaths (%) | 12 (19.4) | 5 (8.1) | 25 (40.3) | 21 (33.9)
Mean Survival Time (years) ^2 (95% CI) | 2.6 (2.4, 2.8) | 2.8 (2.7, 3.0) | 5.5 (4.3, 6.8) | 8.0 (6.9, 9.1)
Difference in Mean Survival Time (years) (95% CI) | -- | 0.24 (-0.03, 0.50) | -- | 2.5 (0.8, 4.1)
Hazard Ratio for Risk of Death ^3 (95% CI) | -- | 0.30 (0.10, 0.89) | -- | 0.40 (0.21, 0.77)
^1 Includes 27 patients in Study 1 and 35 treatment-naïve patients in Study 2.
^2 Based on the area under the survival curves up to 11 years of follow-up.
^3Based on a Cox regression model (with treatment as the only covariate) stratified by continent of residency.
Note: Treated patients were matched 1:1 to untreated patients (who were alive at the age when the treated patient began ZOKINVY) by mutation status (classic/unknown versus non-classic), sex and continent of residence using a fixed 50th percentile matching algorithm. In the fixed 50th percentile matching algorithm, candidate untreated patients were first sorted by decreasing last known age and the candidate in the 50th percentile was selected as the match. Follow-up time for a matched pair of treated and untreated patients began at the age of the treated patient at ZOKINVY initiation.

Figure 1: Kaplan-Meier Survival Curves for Follow-up Time Censored at Last Follow-up for Patients with HGPS

Note: The Kaplan-Meier (KM) survival curve for the ZOKINVY-treated patients is indicated with a solid line; the curve for the untreated patients is indicated with a dashed line. The shaded regions in blue and red represent the 95% confidence bands for the treated and untreated KM survival curves, respectively.

16 HOW SUPPLIED/STORAGE AND HANDLING

ZOKINVY is supplied as:

- 50 mg capsules: Size 4 hard capsule, opaque yellow with “LNF” and “50” printed in black.
  Bottles of 30 capsules each (NDC 42358-450-30)
- 75 mg capsules: Size 3 hard capsule, opaque light orange with “LNF and “75” printed in black.
  Bottles of 30 capsules each (NDC 42358-475-30)

Store at 20°C-25°C (68°F-77°F), excursions permitted to 15°C-30ºC (59°F-86ºF) [see USP Controlled Room Temperature].

17 PATIENT COUNSELING INFORMATION

Advise the patient to read the FDA-approved patient labeling (Patient Information and Instructions for Use).

Dosing [see Dosage and Administration (2.1)]

- Advise patients and caregivers that ZOKINVY should be taken twice daily with the morning and evening meals.
- Inform patients and caregivers that if a dose is missed, the next dose should be given as soon as possible up to 8 hours prior to the next scheduled dose. If less than 8 hours remain before the next scheduled dose, the patient should skip the missed dose and resume taking ZOKINVY at the next scheduled dose.

Preparation and Administration [see Dosage and Administration (2.4), Drug Interactions (7)]

- Advise patients to swallow the capsule whole with water. The capsules should not be chewed.
- For patients unable to swallow capsules, advise patients and caregivers that the contents of ZOKINVY can be mixed with Ora Blend SF or Ora-Plus. For patients unable to access or tolerate Ora Blend SF or Ora-Plus, the contents of ZOKINVY can be mixed with orange juice or applesauce. Advise patients not to mix the contents of ZOKINVY with juice containing grapefruit or Seville oranges. Advise patients and caregivers that the mixture must be prepared fresh for each dose and taken within approximately 10 minutes of mixing.
- Advise patients and caregivers to read and carefully follow the instructions for administering the capsule contents in Ora Blend SF, Ora-Plus, orange juice or applesauce [see Instructions for Use]. Advise patients and caregivers to call their healthcare provider or pharmacist if they have any questions.

QTc Interval Prolongation [see Warnings and Precautions (5.1), Drug Interactions (7.1), Clinical Pharmacology (12.2)]

- Inform patients and caregivers that ZOKINVY causes QTc interval prolongation and may increase the risk of Torsades de pointes, other ventricular arrhythmias, and sudden death.
- Instruct patients or caregivers to notify their healthcare provider if they experience symptoms such as dizziness, lightheadedness, heart palpitations, or loss of consciousness.
- Instruct patients to inform their healthcare provider if they are taking any other medications that may prolong the QTc interval.

Drug Interactions [see Dosage and Administration (2.2, 2.3), Contraindications (4), Warnings and Precautions (5.1, 5.2), Drug Interactions (7.1)]

Inform patients and caregivers that ZOKINVY may interact with several drugs. Advise patients and their caregivers to inform their healthcare provider before starting or discontinuing a prescription or non-prescription drug, supplement, or strong CYP3A inhibitor.

Nephrotoxicity [see Warnings and Precautions (5.4), Nonclinical Toxicology (13.2)]

Inform the patient and caregiver of the risk of kidney damage.

Retinal Toxicity [see Warnings and Precautions (5.5), Nonclinical Toxicology (13.2)]

Inform the patient and caregiver of the risk of developing difficulty with night vision. Advise patients and caregivers to contact their healthcare provider if they experience a change in vision.

Gastrointestinal Adverse Reactions [see Dosage and Administration (2.2), Adverse Reactions (6.1)]

Inform patients and caregivers that gastrointestinal adverse reactions are common with ZOKINVY. These include, but are not limited to, vomiting, diarrhea, and nausea. Advise patients and caregivers to contact their healthcare provider if these adverse reactions persist.

Hypertension [see Adverse Reactions (6.1)]

Inform patients and caregivers that blood pressure may increase while taking ZOKINVY. Symptoms of hypertension may include headaches, shortness of breath, nosebleeds, flushing, dizziness, or chest pain. Advise patients and caregivers to contact their healthcare provider if these adverse reactions occur.

Impaired Fertility [see Warnings and Precautions (5.6), Nonclinical Toxicology (13.1)]

Inform females and males of reproductive potential that ZOKINVY may impact pubertal development and impair fertility.

Embryo-Fetal Toxicity [see Warnings and Precautions (5.7), Use in Specific Populations (8.1, 8.3)]

Inform pregnant women and female patients of reproductive potential of the potential risk to a fetus. Advise females of reproductive potential to use effective contraception during treatment with ZOKINVY.

Manufactured for:
Sentynl Therapeutics, Inc., Solana Beach, CA 92075
ZOKINVY is a registered trademark of Sentynl Therapeutics, Inc.

PATIENT INFORMATION
ZOKINVY® (ZO-kinvy)
(lonafarnib)
capsules, for oral use

What is ZOKINVY?
ZOKINVY is a prescription medicine used to:

- lower the risk of death in adults and children 12 months of age or older with Hutchinson-Gilford Progeria Syndrome (HGPS), who have a certain body surface area.
- treat adults and children 12 months of age or older with certain types of Progeroid Laminopathies, who have a certain body surface area.

ZOKINVY is not for use in people with non-HGPS Progeroid Syndromes or with Progeroid Laminopathies that are processing-proficient.
It is not known if ZOKINVY is safe and effective in children under 12 months of age.

Do not take ZOKINVY if you are taking:

- a strong CYP3A inhibitor
- a strong or moderate CYP3A inducer
- midazolam
- lovastatin, simvastatin, or atorvastatin

Ask your healthcare provider if you are not sure if your medicine may be one that is listed above.

Before taking ZOKINVY, tell your healthcare provider about all of your medical conditions, including if you:

- have a history of QTc interval prolongation or other abnormal heartbeat.
- have slow heartbeat.
- have low magnesium levels or low potassium levels.
- have kidney problems.
- have eye problems.
- are pregnant or plan to become pregnant. ZOKINVY can harm your unborn baby. Females who are able to become pregnant should use effective birth control (contraception) during treatment with ZOKINVY.
- are breastfeeding or plan to breastfeed. It is not known if ZOKINVY can pass into your breast milk. Talk to your healthcare provider about the best way to feed your baby during treatment with ZOKINVY.

Tell your healthcare provider about all the medicines you take, including prescription and over-the-counter medicines, vitamins, and herbal supplements. Taking ZOKINVY with certain other medicines may affect how the other medicines work and other medicines may affect how ZOKINVY works, and may increase your risk of side effects, including a heart rhythm problem called QTc interval prolongation. Especially tell your healthcare provider if you take any other medicines that may cause QTc interval prolongation.
Know the medicines you take. Keep a list of them with you to show your healthcare provider and pharmacist when starting a new medicine.

How should I take ZOKINVY?

- Take ZOKINVY exactly as your healthcare provider tells you to.
- Do not stop taking ZOKINVY without talking to your healthcare provider. Your healthcare provider may change your dose of ZOKINVY if needed.
- Your healthcare provider will prescribe your dose of ZOKINVY based on your body size (height and weight).
- Take ZOKINVY 2 times a day with morning and evening meals.
- Swallow ZOKINVY capsules whole with an adequate amount of water. Do not chew ZOKINVY capsules.
- If you or your child cannot swallow the ZOKINVY capsule whole, see the detailed Instructions for Use that comes with ZOKINVY for information about how to prepare and give or take a dose of ZOKINVY by mixing the contents of a ZOKINVY capsule with either Ora Blend SF, Ora-Plus, orange juice, or applesauce.
- Each dose of ZOKINVY mixture must be prepared fresh and taken within about 10 minutes of mixing.
- Do not take ZOKINVY with any juice that contains grapefruit or Seville oranges. Seville oranges may also be called bitter or sour oranges.
- If you miss a dose of ZOKINVY, take it as soon as possible up to 8 hours before your next scheduled dose with food. If it is less than 8 hours before your next dose of ZOKINVY, skip the missed dose and take ZOKINVY at your next regularly scheduled dose.

What are the possible side effects of ZOKINVY?
ZOKINVY may cause serious side effects, including:

- A serious heart rhythm problem called QTc Interval Prolongation. This condition can cause an abnormal heartbeat in people who take ZOKINVY and may lead to death. Your healthcare provider should check your heart and do blood tests before and during treatment with ZOKINVY. Tell your healthcare provider right away if you feel dizzy, lightheaded, faint, or have a change in your heartbeat (a fast or irregular heartbeat).
- Severe kidney problems. ZOKINVY may cause severe kidney problems. Your healthcare provider will monitor your kidney function regularly during treatment with ZOKINVY.
- Eye problems. ZOVINKY may cause problems with night vision. Call your healthcare provider right away if you develop any new changes in your vision.

The most common side effects of ZOKINVY include:

- vomiting
- diarrhea
- infection
- nausea
- decreased appetite
- tiredness
- upper respiratory tract infection
- stomach-area (abdominal) pain
- muscle and joint (musculoskeletal) pain

- electrolyte abnormalities
- decreased weight
- headache
- myelosuppression
- increased liver enzyme blood test results
- decreased blood bicarbonate
- cough
- hypertension

Call your healthcare provider if you continue to have nausea, vomiting or diarrhea that leads to loss of appetite and weight loss during your treatment with ZOKINVY.
ZOKINVY may cause an increase in your blood pressure (hypertension). Your healthcare provider will check your blood pressure during treatment with ZOKINVY. Call your healthcare provider right away if you develop any symptoms of high blood pressure including headaches, shortness of breath, nosebleeds, flushing, tiredness, dizziness, vision problems, irregular heartbeat, or chest pain.
ZOKINVY may cause fertility problems in females and males, which may affect your ability to have children. Talk to your healthcare provider if you have concerns about fertility.
These are not all of the possible side effects of ZOKINVY.
Call your doctor for medical advice about side effects. You may report side effects to FDA at 1-800-FDA-1088. You may also report side effects to Sentynl Therapeutics, Inc. at 1-888-507-5206 or zokinvysafety@sentynl.com.

How should I store ZOKINVY?

- Store at room temperature between 68°F to 77°F (20°C to 25°C).

Keep ZOKINVY and all medicines out of reach of children.

General information about the safe and effective use of ZOKINVY
Medicines are sometimes prescribed for purposes other than those listed in the Patient Information. Do not use ZOKINVY for a condition for which it was not prescribed. Do not give ZOKINVY to other people, even if they have the same symptoms that you have. It may harm them. You can ask your healthcare provider or pharmacist for information about ZOKINVY that is written for health professionals.

What are the ingredients in ZOKINVY?
Active ingredient: lonafarnib.
Inactive ingredients: croscarmellose sodium, magnesium stearate, poloxamer 188, povidone, and silicon dioxide.
The capsule shell (ZOKINVY 50 mg hard capsule) contains: gelatin, titanium dioxide and yellow iron oxide.
The capsule shell (ZOKINVY 75 mg hard capsule) contains: gelatin, titanium dioxide, yellow iron oxide and red iron oxide.
The printing ink contains: ammonia solution, black iron oxide, butyl alcohol, dehydrated alcohol, isopropyl alcohol, potassium hydroxide, propylene glycol, purified water, and shellac.
Manufactured for: Sentynl Therapeutics, Inc., Solana Beach, CA 92075
©2024 Sentynl Therapeutics, Inc.
For more information call Sentynl Therapeutics at 1-888-251-2800 or visit www.zokinvy.com or www.sentynl.com

This Patient Information has been approved by the U.S. Food and Drug Administration.

Revised: 7/2025

INSTRUCTIONS FOR USE

ZOKINVY® (ZO-kinvy) (lonafarnib)

capsules, for oral use

This Instructions for Use contains information on how to mix and give or take a dose of ZOKINVY if the capsules cannot be swallowed whole.

Read this Instructions for Use before you start giving or taking ZOKINVY and each time you get a refill. There may be new information. This information does not take the place of talking to your healthcare provider about you or your child's medical condition or treatment

Supplies needed to prepare and give or take a dose of ZOKINVY

Before mixing a dose of ZOKINVY, gather the following supplies:

- the prescribed number of ZOKINVY capsules for you or your child's dose. Place the capsule or capsules on a clean flat surface.
- either Ora-Blend SF, Ora-Plus, orange juice or applesauce for mixing. Do not mix with juice that contains grapefruit or Seville oranges. Seville oranges may also be called bitter or sour oranges.
- if mixing with Ora-Blend SF, Ora-Plus or orange juice: a clean medicine cup with 5 milliliter (mL) and 10 mL measurement levels, OR if mixing with applesauce: a clean teaspoon.
- clean cup(s) for each ZOKINVY capsule to be mixed.
- a clean spoon for stirring the mixture.

How to open ZOKINVY capsules and mix the capsule contents

Step 1:

If mixing with Ora-Blend SF, Ora-Plus or orange juice: Use a clean medicine cup to measure either 5 mL or 10 mL of Ora-Blend SF, Ora-Plus or orange juice.

If mixing with applesauce: measure either 1 or 2 teaspoonfuls of applesauce.

You can choose to use 5 mL or 10 mL of liquid or 1 or 2 teaspoonfuls of applesauce (See Figure A).

Step 2:

Place the Ora-Blend SF, Ora-Plus, orange juice or applesauce measured in Step 1 into a clean cup (See Figure B).

Step 3:

Hold a ZOKINVY capsule above the clean cup containing the liquid or applesauce. Hold the ZOKINVY capsule on both sides between your thumb and forefinger. Gently twist and pull apart the capsule (See Figure C). Empty the contents of the capsule directly into the clean cup (See Figure D).

Step 4:

Using a clean spoon, mix the ZOKINVY capsule contents well (See Figure E). If only 1 capsule is to be taken, skip to Step 6. If 2 capsules are to be taken, go to Step 5.

Step 5:

If 2 capsules will be taken, repeat Steps 1 through 4 for the second capsule. After completing the mixing process for the second capsule, the 2 servings can either be placed together in a single cup or remain in 2 serving cups for you or your child to take the full dose of ZOKINVY. After you finish, go to Step 6.

Step 6:

Give or take all of the ZOKINVY mixture with morning and evening meals within about 10 minutes of preparing.

How should I store ZOKINVY?

- Store at room temperature between 68°F to 77°F (20°C to 25°C)

Keep ZOKINVY and all medicines out of reach of children.

This Instructions for Use has been approved by the U.S. Food and Drug Administration. Manufactured for:

Sentynl Therapeutics, Inc.,
420 Stevens Ave., Suite 200
Solana Beach, CA 92075

©2024 Sentynl Therapeutics, Inc.
Revised: 7/2025

Principal Display Panel - 50 mg Carton Label

NDC 42358-450-30

Zokinvy
(lonafarnib) capsules

50 mg

30 capsules

Rx only

Principal Display Panel - 50 mg Bottle Label

NDC 42358-450-30

Zokinvy
(lonafarnib) capsules

50 mg

Rx only

30 capsules

Principal Display Panel - 75 mg Carton Label

NDC 42358-475-30

Zokinvy
(lonafarnib) capsules

75 mg

30 capsules

Rx only

Principal Display Panel - 75 mg Bottle Label

NDC 42358-475-30

Zokinvy
(lonafarnib) capsules

75 mg

Rx only

30 capsules